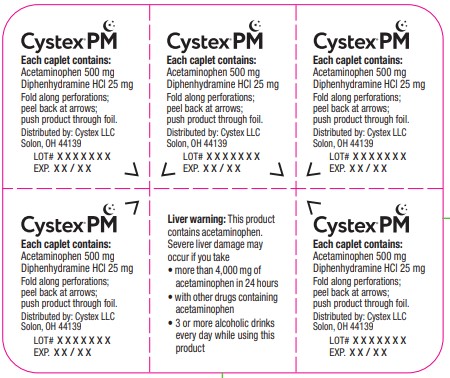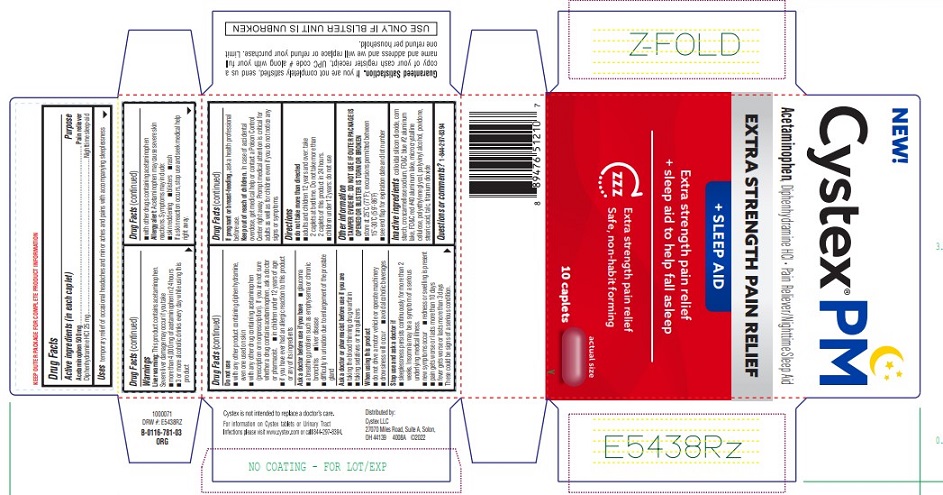 DRUG LABEL: Cystex 

NDC: 69693-417 | Form: TABLET
Manufacturer: Clarion Brands, LLC
Category: otc | Type: HUMAN OTC DRUG LABEL
Date: 20251227

ACTIVE INGREDIENTS: ACETAMINOPHEN 500 mg/1 1; DIPHENHYDRAMINE HYDROCHLORIDE 25 mg/1 1
INACTIVE INGREDIENTS: SILICON DIOXIDE; STARCH, CORN; CROSCARMELLOSE SODIUM; FD&C BLUE NO. 2--ALUMINUM LAKE; FD&C RED NO. 40; MICROCRYSTALLINE CELLULOSE; POLYETHYLENE GLYCOL, UNSPECIFIED; POLYVINYL ALCOHOL, UNSPECIFIED; POVIDONE, UNSPECIFIED; STEARIC ACID; TALC; TITANIUM DIOXIDE

Drug Facts

Active ingredients (in each caplet)

Acetaminophen 500 mg
Diphenhydramine HCl 25 mg

Purpose

Acetaminophen 500 mg............................................................... Pain reliever
Diphenhydramine HCl 25 mg ...............................................Nighttime sleep-aid

INDICATIONS AND USAGE

Uses temporary relief of occasional headaches and minor aches and pains with accompanying sleeplessness

Warnings

Liver warning:This product contains acetaminophen. Severe liver damage may occur if you take

- more than 4,000 mg of acetaminophen in 24 hours
- 3 or more alcoholic drinks every day while using this product
- with other drugs containing acetaminophen

Allergy alert:Acetaminophen may cause severe skin reactions. Symptoms may include:

- skin reddening
- blisters
- rash

If a skin reaction occurs, stop use and seek medical help right away.

Do not use

- with any other product containing diphenhydramine, even one used on skin
- with any other drug containing acetaminophen (prescription or nonprescription). If you are not sure whether a drug contains acetaminophen, ask a doctor or pharmacist.
- in children under 12 years of age
- if you have ever had an allergic reaction to this product or any of its ingredients

Ask a doctor before use if

- glaucoma
- a breathing problem such as emphysema or chronic bronchitis
- liver disease
- difficulty in urination due to enlargement of the prostate gland

Ask a doctor or pharmacist before use if you are

- taking the blood thinning drug warfarin
- taking sedatives or tranquilizers

When using this product

- do not drive a motor vehicle or operate machinery
- drowsiness will occur
- avoid alcoholic beverages

Stop use and ask a doctor if

- sleeplessness persists continuously for more than 2 weeks. Insomnia may be a symptom of a serious underlying medical illness.
- new symptoms occur
- redness or swelling is present
- pain gets worse or lasts more than 10 days
- fever gets worse or lasts more than 3 days

These could be signs of a serious condition.

PREGNANCY OR BREAST FEEDING

If pregnant or breast feeding,ask a health professional before use.

Keep out of reach of children

In case of accidental overdose, get medical help or contact a Poison Control Center right away. Prompt medical attention is critical for adults as well as for children even if you do not notice any signs or symptoms.

Directions

- do not take more than directed
- adults and children 12 years and over: take 2 caplets at bedtime. Do not take more than 2 caplets of this product in 24 hours.
- children under 12 years: do not use

Other information

- TAMPER EVIDENT: DO NOT USE IF OUTER PACKAGE IS OPENED OR BLISTER IS TORN OR BROKEN
- store at 25°C (77°F); excursions permitted between 15°-30°C (59°-86°F)
- see end flap for expiration date and lot number

Inactive ingredients

colloidal silicon dioxide, corn starch, croscarmellose sodium, FD&C blue #2 aluminum lake, FD&C Red #40 aluminum lake, microcrystalline cellulose, polyethylene glycol, polyvinyl alcohol, povidone, stearic acid, talc, titanium dioxide

Questions or comments?

1-844-297-8394

PRINCIPAL DISPLAY PANEL

NEW!
Cystex® PM
Acetaminophen , Diphenhydramine HCL • Pain Reliever/Nighttime Sleep Aid
EXTRA STRENGTH PAIN RELIEF
+ SLEEP AID
Extra strength pain relief
+ sleep aid to help fall asleep
ZZZ
Extra strength pain relief
Safe, non-habit forming
10 caplets
actual size
Guaranteed Satisfaction. If you are not completely satisfied, send us a copy of your cash register receipt, UPC code # along with your full name and address and we will replace or refund your purchase. Limit one refund per household.
USE ONLY IF BLISTER UNIT IS UNBROKEN
Cystex is not intended to replace a doctor's care.
For more information on Cystex tablets or Urinary Tract
Infections please visit www.cystex.com or call 844-297-8394.
Distributed by:
Cystex LLC
27070 Miles Road, Suite A Solon,
OH 44139 4008A ©2022

Cystex® PM
Each caplet contains:
Acetaminophen 500 mg
Diphenhydramine HCL 25 mg
Fold along perforations;
peel back at arrows;
push product through foil.
Distributed by: Cystex LLC
Solon, OH 44139
Lot# XXXXXXX
EXP. XX / XX
Liver warning: This product
contains acetaminophen.
Severe liver damage may
occur if you take
● more than 4,000 mg of acetaminophen in 24 hours
● with other drugs containing acetaminophen
● 3 or more alcoholic drinks every day while using this product